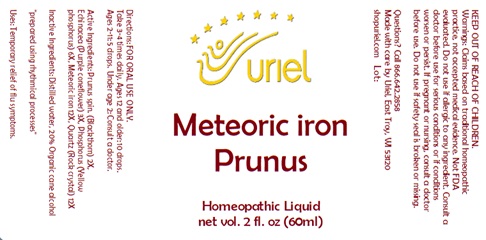 DRUG LABEL: Meteoric Iron Prunus
NDC: 48951-7054 | Form: LIQUID
Manufacturer: Uriel Pharmacy Inc.
Category: homeopathic | Type: HUMAN OTC DRUG LABEL
Date: 20240326

ACTIVE INGREDIENTS: SLOE 2 [hp_X]/1 mL; ECHINACEA, UNSPECIFIED 3 [hp_X]/1 mL; PHOSPHORUS 6 [hp_X]/1 mL; IRON 12 [hp_X]/1 mL; SILICON DIOXIDE 12 [hp_X]/1 mL
INACTIVE INGREDIENTS: WATER; ALCOHOL

Meteoric Iron Prunus

INDICATIONS AND USAGE

Directions: FOR ORAL USE ONLY.

DOSAGE AND ADMINISTRATION

Take 3-4 times daily. Ages 12 and older: 10 drops. Ages 2-11: 5 drops. Under age 2: Consult a doctor.

Active Ingredients: Prunus spin. (Blackthorn) 2X,
Echinacea (Purple coneflower) 3X, Phosphorus (Yellow phosphorus) 6X, Meteoric iron 12X, Quartz (Rock crystal) 12X

Inactive Ingredients: Distilled water, Organic cane alcohol

prepared using rhythmical processes

PURPOSE

Uses: Temporary relief of flu symptoms.

KEEP OUT OF REACH OF CHILDREN.

WARNINGS

Warnings: Claims based on traditional homeopathic practice, not accepted medical evidence. Not FDA evaluated. Do not use if allergic to any ingredient. Consult a doctor before use for serious conditions or if conditions worsen or persist. If pregnant or nursing, consult a doctor before use. Do not use if safety seal is broken or missing.

QUESTIONS

Questions? Call 866.642.2858 Made with care by Uriel, East Troy, WI 53120 shopuriel.com Lot: